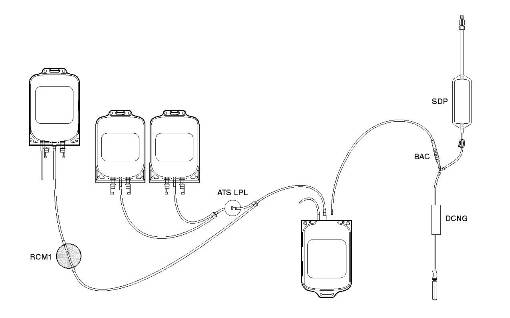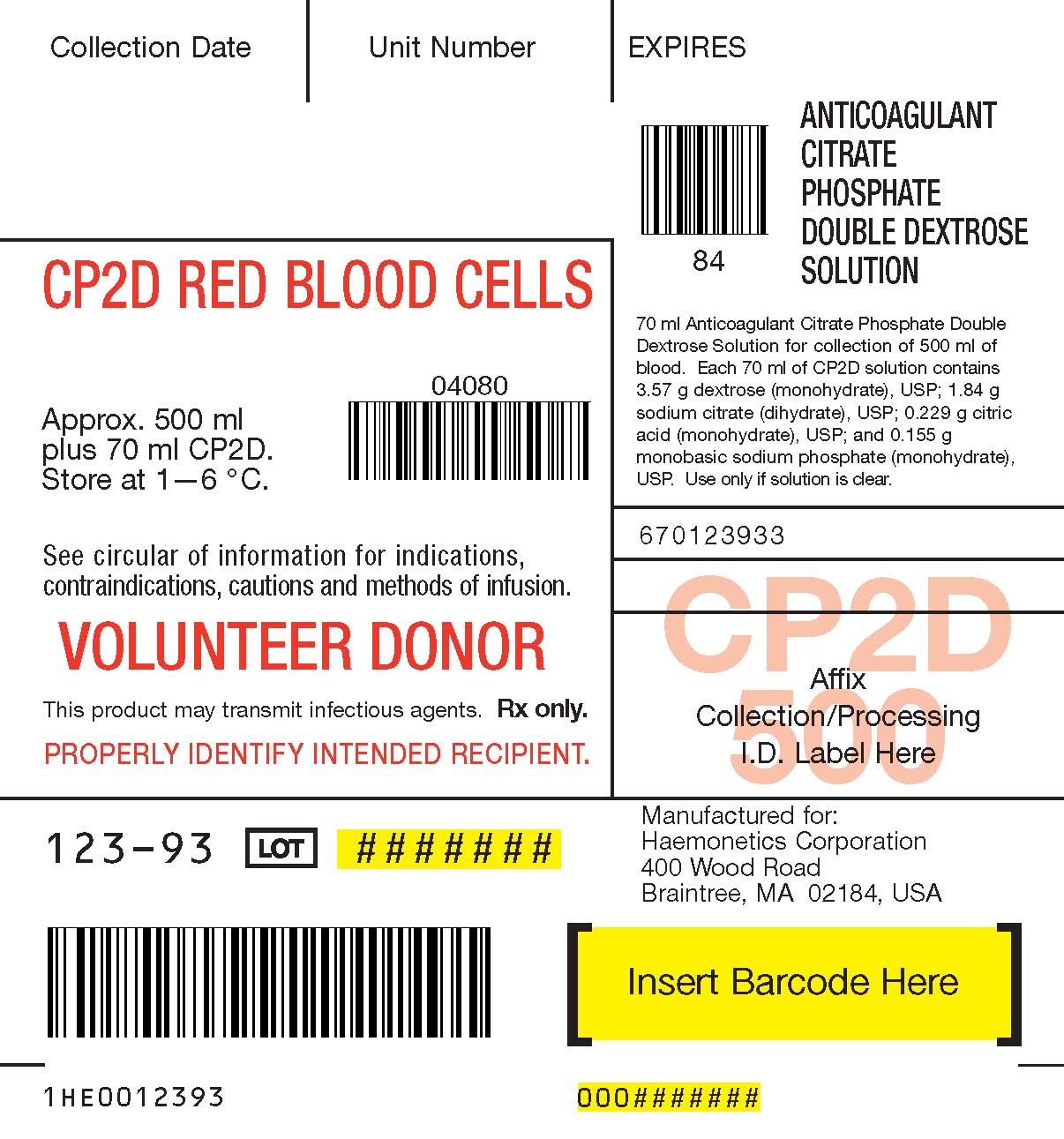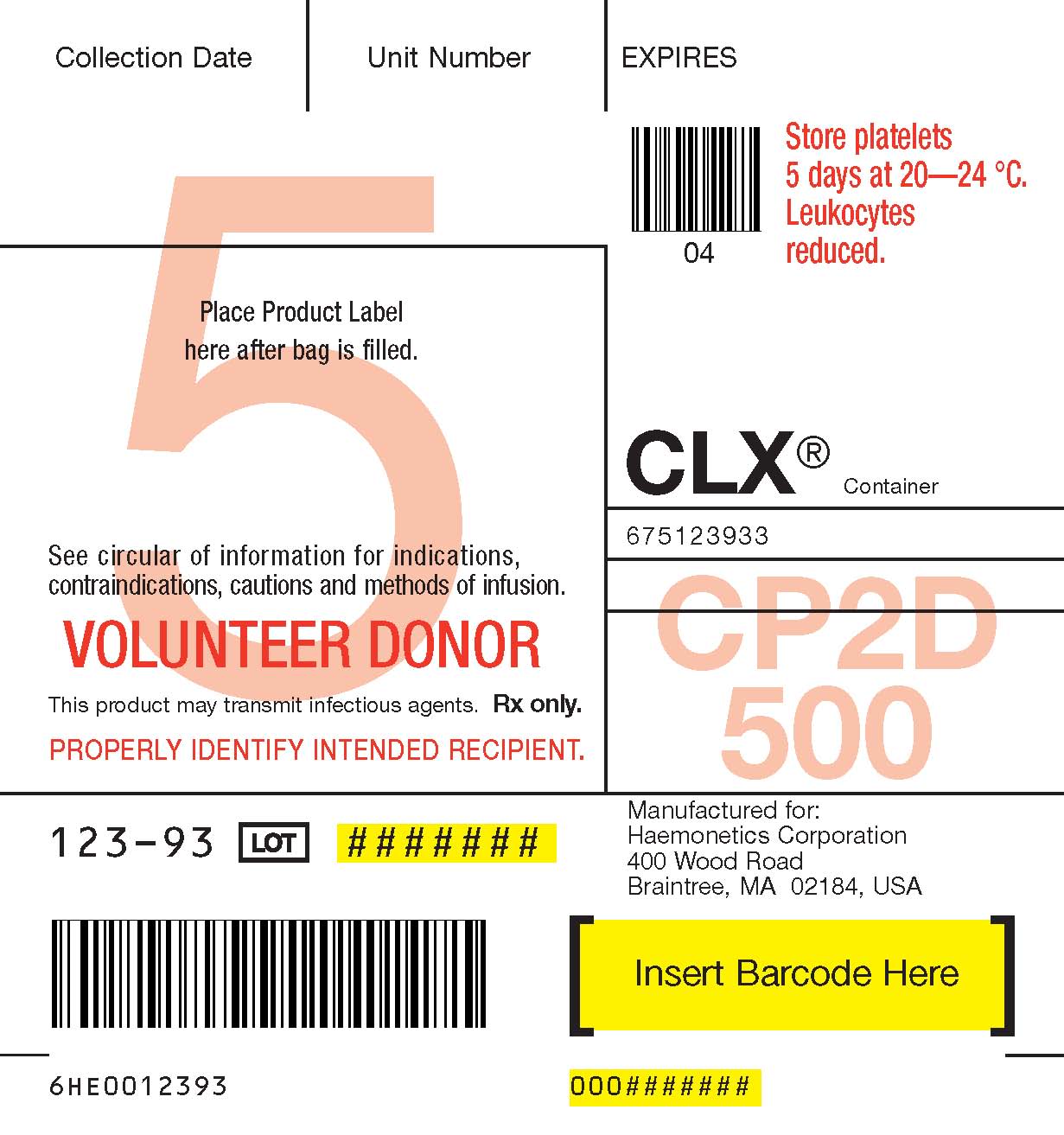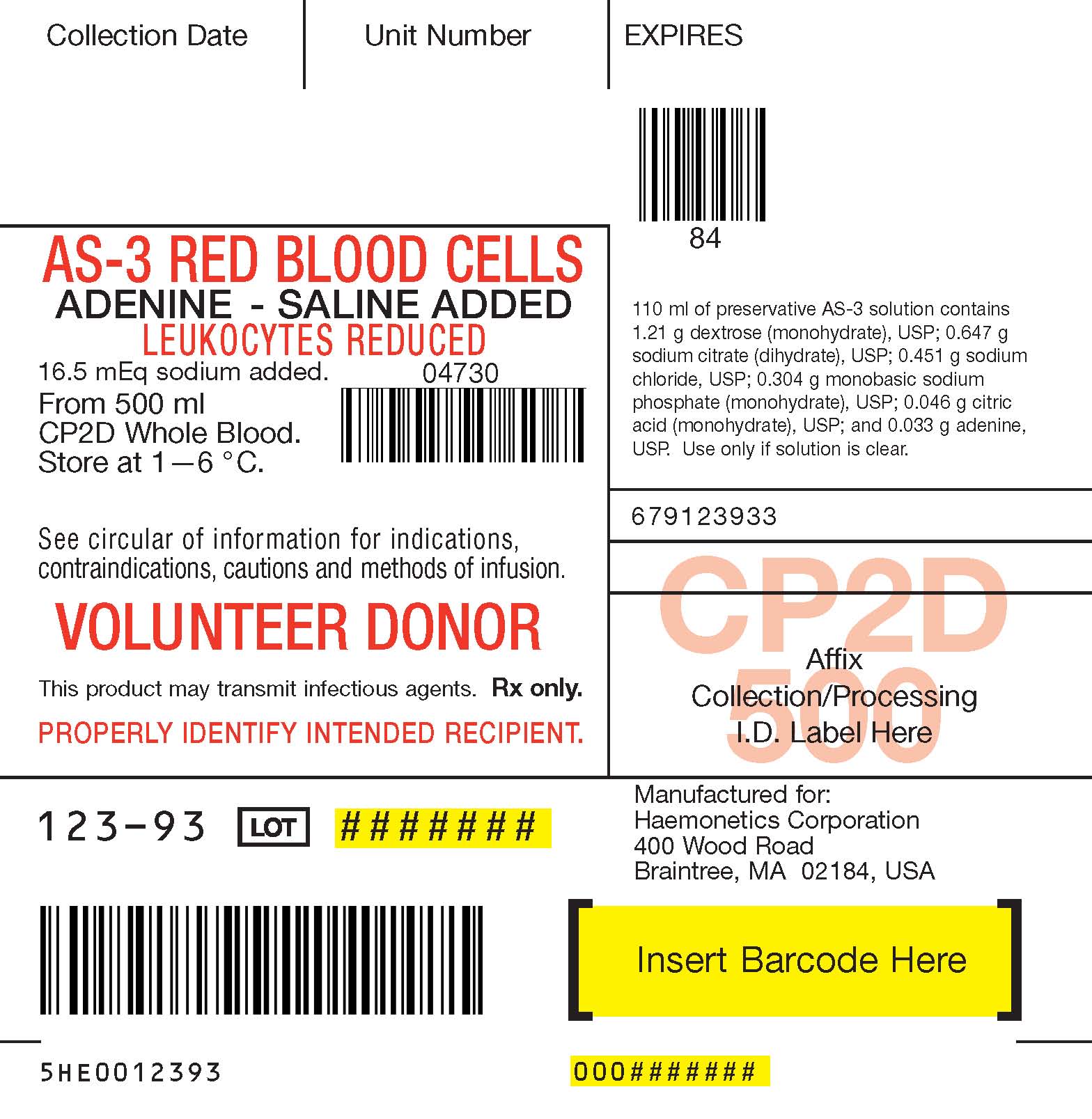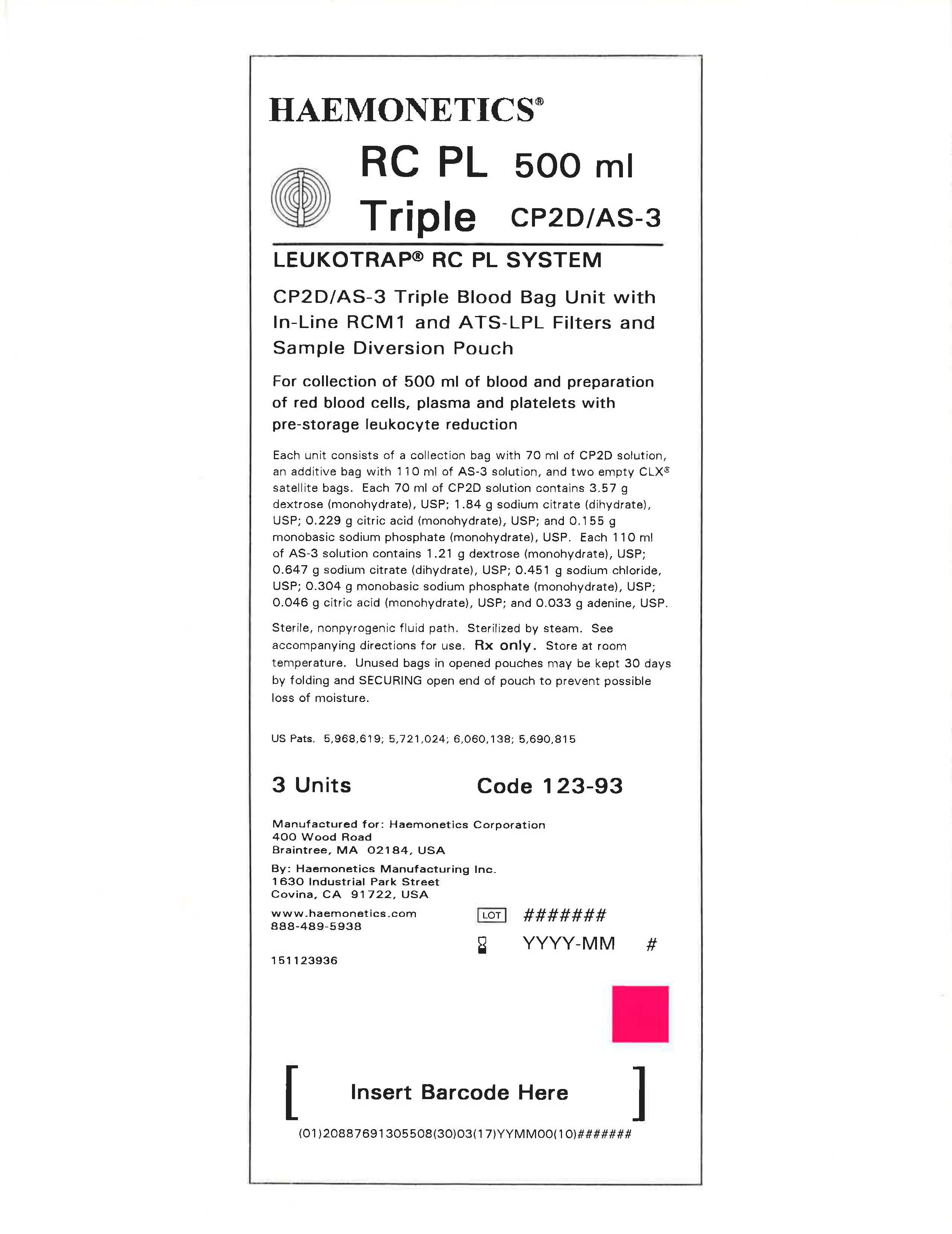 DRUG LABEL: Leukotrap - CP2D Solution
NDC: 53157-123 | Form: SOLUTION
Manufacturer: Haemonetics Manufacturing Inc.
Category: prescription | Type: HUMAN PRESCRIPTION DRUG LABEL
Date: 20250102

ACTIVE INGREDIENTS: DEXTROSE, UNSPECIFIED FORM 3.57 g/70 mL

Leukotrap RC PL System

CP2D/AS-3 BLOOD BAG UNIT WITH IN-LINE RCM1 AND ATS-LPL FILTERS AND SAMPLING SYSTEM

For collection of blood and preparation of red blood cells, plasma and platelets with pre-storage leukocyte reduction.

Instruction for Use for Systems Containing a Y Sampling Site (YSS) or Sample Diversion Pouch (with or without a pre-attached SampLok™ Vacuum Tube Holder).

Refer to unit foil package label for specific product description being used.

Sterile, non-pyrogenic fluid path. Sterilized by steam.

Rx only.

CLINICAL PHARMACOLOGY

This product is free of natural rubber latex.

Illustration

Collection system with sample diversion pouch

INDICATIONS AND USAGE

Whole blood; for use in blood collection.

CONTRAINDICATIONS

None known.

WARNINGS

Failure to achieve and maintain a closed system during processing would result in a product that must be transfused within 24 hours.

GENERAL PRECAUTIONS

Use aseptic technique.

Use only if solutions are clear.

Maximum hard spin conditions for RCM1 filter should not exceed 5000 g.

If using centrifuge cups with filter adapters, the RCM1 filter should not be placed within the adapter when hard spin conditions are used.

Do not exceed maximum head heights as indicated within the processing instructions.

Filtration can begin at room temperature up to 8 hours, or 1—6 °C up to 24 hours post-collection. Filtration must begin within 24 hours of collection.

If preparing a platelet concentrate, the platelet-rich plasma should be separated from the red blood cells within 8 hours after collection.

If preparing fresh frozen plasma, separate from the red cells and place in the freezer at -18 °C or colder within 8 hours after blood collection.

For systems with in-line breakaway closure (BAC), use oval style centrifuge cups.

Increased (mechanical) hemolysis has been associated with stripping when blood is cold and has a higher hematocrit. Do not strip forcefully or frequently against a snap-open closure if re-suspension of segmented tubing is necessary.

ADVERSE REACTIONS

No adverse reactions specifically attributable to this drug have been reported.

HOW SUPPLIED

* During processing, always observe the following precautions:

1. Sealing should be done in a manner that avoids fluid splatter.

2. Always dispose of blood-contaminated products in a manner consistent with established BIOHAZARD safety procedures

Instructions for Use

I. Blood Collection Instructions for Systems Containing a Y Sampling Site (YSS) Only

1. Load blood agitation device or suspend blood bag on donor scale and adjust donor scale to desired collection gross weight as per manufacturer's instructions.

2. Clamp donor tubing between the DonorCare™ Needle Guard (DCNG) and Y Sampling Site.

3. Secure donor tubing above the Y connector and disinfect site of phlebotomy.

4. If using blood pressure cuff, inflate to not more than 60 mm Hg.

5. Remove donor needle cover and accomplish phlebotomy.

6. Release clamp and ensure there is blood flow. Reduce pressure as required.

7. Slide the DCNG midway over the needle hub and securely tape DCNG to the donor's arm as close to top of the DCNG as possible. Note: If blood flow is slow, slide DCNG away from the needle hub, adjust and re-engage DCNG. If repeated needle adjustment is necessary, slide DCNG away from the needle hub and re-engage at the end of blood collection.

8. Collect appropriate volume of blood into collection bag, as indicated on packaging. Note: Mix blood and anticoagulant frequently during collection to avoid possible clot formation. For example: once every 45 seconds and immediately after collection. If blood agitation device is used, follow manufacturer's operating instructions.

9. After required amount of blood has been collected, seal donor tubing between the Y Sampling Site and the collection bag.* Note: If pre-filtration quality control is to be performed, leave an adequate length (~10 inches) of QC tubing containing anticoagulated blood attached to the collection bag.

10. For blood sampling, remove the Y Sampling Site needle cover. Ensure the protective sheath is in place over the sampling needle.

11. Fasten the vacuum tube holder on to the base of the sampling needle.

12. Collect blood samples into vacuum tubes.

13. Ensure the vacuum tubes are centered within the vacuum holder during sample collection.

14. Maintain forward pressure on the vacuum tubes during sample collection. Note: After the last tube is collected, it is recommended that the vacuum tube holder be left in place to prevent an accidental needlestick.

15. After blood samples are collected, clamp donor tubing between the Y Sampling Site and DCNG, as close as possible to the DCNG.

16. Release any remaining pressure from the donor's arm.

17. DCNG must be held stationary while the needle is withdrawn into it. While holding sides of DCNG near the front, grasp the tubing below the clamp and pull the needle into the DCNG until it locks into place, and the needle hub engages the bottom of the DCNG.

18. Insert the DCNG into the vacuum tube holder. Note: It is recommended that the DCNG be inserted securely into the vacuum tube holder, prior to discarding.

19. Seal donor tubing adjacent to DCNG.* Detach and discard needle, DCNG, Y Sampling Site and tubing.*

20. Strip tubing between seal and collection bag.

21. Continue to "Blood Processing and Filtration Instructions," Section IV, Step 1.

II. Blood Collection Instructions for Systems Containing a Sample Diversion Pouch with or without a pre-attached SampLok™ Vacuum Tube Holder

When using systems with a pre-attached SampLok™ vacuum tube holder, follow instructions as noted below, but refer to Section III when indicated to do so.

1. Load blood agitation device or suspend blood bag on donor scale and adjust donor scale to desired collection gross weight as per manufacturer's instructions.

2. Clamp donor tubing between the DonorCare™ Needle Guard (DCNG) and Sampling Site.

3. Secure donor tubing above the Y connector and disinfect site of phlebotomy.

4. If using blood pressure cuff, inflate to not more than 60 mm Hg.

5. Remove donor needle cover and accomplish phlebotomy.

6. Release clamp, and ensure there is blood flow.

7. Slide the DCNG midway over the needle hub and securely tape DCNG to the donor's arm as close to the top of the DCNG as possible. Note: If blood flow is slow, slide DCNG away from the needle hub, adjust and re-engage DCNG. If repeated needle adjustment is necessary, slide DCNG away from the needle hub and re-engage at the end of blood collection.

8. The donor blood will be automatically diverted to the sample diversion pouch. Once the sample diversion pouch is filled, close clamp immediately on tubing between the sample diversion pouch and Y connector. Warning: To avoid risk of air embolism to donor, do not squeeze sample diversion pouch while tubing is open.

9. Open snap-open closure between the Y connector and the collection bag to initiate blood collection. Reduce pressure as needed.

10. Permanently seal tubing between the sample diversion pouch and the Y connector to maintain sterility of the system prior to collecting blood samples.* Note: When using systems with a pre-attached SampLok™ vacuum tube holder, go to Section III.

11. For blood sampling, remove the Sampling Site needle cover. Ensure the protective sheath is in place over the sampling needle.

12. Fasten the vacuum tube holder on to the base of the sampling needle.

13. Position the sample diversion pouch downward so that the air rises to the top of the pouch and away from the vacuum tube holder.

Notes:

• Drawing air into the vacuum tube may cause hemolysis.

• Collect blood samples from the sample diversion pouch into vacuum tubes within approximately four minutes to avoid possible clot formation.

14. Ensure the vacuum tubes are centered within the vacuum tube holder during sample collection.

15. Maintain forward pressure on the vacuum tube during sample collection. Note: After the last tube is collected, it is recommended that the vacuum tube holder be left in place.

16. Collect appropriate volume of blood into collection bag as indicated on packaging. Note: Mix blood and anticoagulant frequently during collection to avoid possible clot formation, for example, once every 45 seconds, and immediately after collection. If blood agitation device is used, follow manufacturer's operating instructions.

17. After required amount of blood has been collected, seal donor tubing between snap-open closure and collection bag.* Note: If pre-filtration quality control is to be performed, leave an adequate length (~10 inches) of QC tubing containing anticoagulated blood attached to the collection bag.

18. Clamp donor tubing between the Y connector and DCNG, as close as possible to the DCNG.

19. Release any remaining pressure from donor's arm.

20. DCNG must be held stationary while the needle is withdrawn into it. While holding sides of DCNG near the front, grasp the tubing below the clamp and pull the needle into the DCNG until it locks into place, and the needle hub engages the bottom of the DCNG.

21. Insert the DCNG into the vacuum tube holder, if desired. Note: It is recommended that the DCNG be inserted securely into the vacuum tube holder, prior to discarding.

22. Seal donor tubing adjacent to DCNG.* Detach and discard needle, DCNG, sample diversion pouch, and tubing.*

23. Strip tubing between seal and collection bag.

24. Continue to "Blood Processing and Filtration Instructions", Section IV, Step 1.

III. When Using Systems with a Pre-attached SampLok Vacuum Tube Holder

1. To collect blood samples, open lid from SampLok™ vacuum tube holder.

2. Open snap-open closure between sample diversion pouch and SampLok™ vacuum tube holder.

3. Position the sample diversion pouch downward so that the air rises to the top of the pouch and away from the SampLok™ vacuum tube holder.

Notes:

• Drawing air into the vacuum tube may cause hemolysis.

• Collect blood samples from the sample diversion pouch into vacuum tubes within approximately four minutes to avoid possible clot formation.

4. Ensure the vacuum tubes are centered within the SampLok™ vacuum tube holder during sample collection.

5. Maintain forward pressure on the vacuum tube during sample collection.

6. The lid may be closed on the SampLok™ vacuum tube holder after sample collection.

7. Return to Section II, Step 17. Note: When collection of unit is complete, and the donor needle is engaged in the DCNG, open the lid of the SampLok™ vacuum tube holder and insert the DCNG into the holder. Twist until it locks into place. An audible click will confirm that it is locked.

IV. Blood Processing and Filtration Instructions

1. Load unit into centrifuge cup [for systems with in-line breakaway closure (BAC), use oval style centrifuge cups], ensuring that the tubing stays in the top half of the cup. Position the platelet (smaller) filter on top of the tubing assembled inside the cup. Place the red blood cell (larger) filter in a horizontal position on top of the entire assembly and secure with tape or Leukotrap Strap. If using centrifuge cups with filter adapters, follow manufacturer's instructions for use.

2. Centrifuge unit per standard protocol.

3. Carefully remove the unit from the centrifuge and place the collection bag in the plasma expressor.

4. Gently apply expressor pressure.

5. Place platelet (smaller) filter on work surface or in Pall® PL holder ensuring that the side labeled "OUT" faces up. Clamp tubing between the red blood cell (larger) filter and the Y connector.

6. Clamp tubing to extra satellite bag.

7. Open snap-open closure of the collection bag and express platelet-rich plasma into a satellite bag.

8. When the outlet side of the platelet filter turns pink, or red blood cells are visible in the tubing between the filter outlet and the Y connector closest to the satellite bags, clamp tubing between the filter and the Y connector closest to the satellite bags. Release expressor pressure.

Notes:

• Do not apply extra pressure to increase flow rate.

• The ATS-LPL filter will not prevent red blood cells from passing into the satellite bag during expression.

9. Seal tubing between platelet filter and the Y connector closest to the satellite bags.* Detach and set aside the platelet-rich plasma for further processing.*

10. Seal tubing between platelet filter and the remaining Y connector.* Detach and discard the platelet filter and tubing.*

11. Hang the AS-3 red blood cell bag in a manner ensuring the filter is in a vertical position. Remove clamp near red blood cell filter. Open snap-open closure of the bag containing Nutricel AS-3 additive solution, and transfer additive solution to the collection bag. Note: Nutricel AS-3 solution should be added to the collection bag immediately after platelet-rich plasma removal.

12. Transfer AS-3 solution under one of the following conditions:

A. Within 8 hours of collection if whole blood is held at room temperature.

B. Within 24 hours of collection if whole blood is refrigerated.

13. Clamp tubing close to the collection bag in order to avoid the introduction of air into the filter.

14. Mix red blood cells gently and thoroughly.

15. Hang the collection bag at one of the following heights, while ensuring that the filter is hanging in the vertical position:

A. No more than 60 inches for blood stored and filtered at room temperature.

B. No more than 76 inches for blood stored and filtered at 1—6 °C.

16. Remove clamp to allow red blood cells to gravity flow through the filter and into the red cell storage bag.

Notes:

• Do not apply mechanical or manual pressure to increase flow rate.

• If unit has not completely filtered by 8 hours post-collection at room temperature, filtration must be completed at 1—6 °C.

• Filtration at maximum head height may shorten filtration times.

• Filtration of red cells can be unattended.

• Filtration times can be influenced by collection and processing conditions and biological variability of donors. Experimental data with some filter products indicate that a prolonged filtration can be an indication of sub-optimal leukocyte reduction.

17. Clamp tubing near red cell storage bag and seal tubing below the filter.* The numbered tubing downstream of the filter will not drain.

Notes:

• If the filter housing (downstream side) and numbered tubing below the filter have drained (emptied) after filtration, it is recommended to perform QC on the unit.

• Do not strip tubing prior to sealing the tubing below the filter. If it is desired to strip blood from numbered tubing, do so only after tubing has been sealed close to the filter and detached.

• If it is necessary to strip blood from numbered tubing for re-suspension, care should be taken when stripping is performed. Increased (mechanical) hemolysis has been associated with stripping when blood is cold and has a higher hematocrit. Do not strip forcefully or frequently against a snap-open closure.

18. Detach and discard collection bag and filter.*

19. If desired, seal at or adjacent to "X" marks on tubing to provide numbered segments of anticoagulated blood for typing or cross matching.* If quality control is to be performed on post-filtration sample, use the attached QC line on the bag containing red cells.

20. Store CP2D/AS-3 preserved red blood cells at 1—6 °C for up to 42 days and use as indicated.

MANUFACTURER

Manufactured for: Haemonetics Corporation

400 Wood Road

Braintree, MA 02184, USA

By: Haemonetics Manufacturing Inc.

1630 Industrial Park Street

Covina, CA 91722, USA

Visit us at www.haemonetics.com

Phone: 888-489-5938

PACKAGE LABEL – PRINCIPAL DISPLAY PANEL

Leukotrap® RC System

CP2D/AS-3 Triple Blood Bag Unit with In-Line RCM1 and ATS-LPL Filters and Sample Diversion Pouch

For collection of 500 ml of blood and preparation of red blood cells, plasma or platelets with pre-storage leukocyte reduction of red blood cells.

Each unit consists of a collection bag with 70 ml of CP2D solution, an additive bag with 110 ml of AS-3 solution, and two empty CLX® satellite bags. Each 70 ml of CP2D solution contains 3.57 g dextrose (monohydrate), USP; 1.84 g sodium citrate (dihydrate), USP; 0.229 g citric acid (monohydrate), USP; and 0.155 g monobasic sodium phosphate (monohydrate), USP. Each 110 ml of AS-3 solution contains 1.21 g dextrose (monohydrate), USP; 0.647 g sodium citrate (dihydrate), USP; 0.451 g sodium chloride, USP; 0.304 g monobasic sodium phosphate (monohydrate), USP; 0.046 g citric acid (monohydrate), USP; and 0.033 g adenine, USP.

Sterile, nonpyrogenic fluid path. Sterilized by steam. See accompanying directions for use. Rx only. Store at room temperature. Unused bags in opened pouches may be kept 30 days by folding and SECURING open end of pouch to prevent possible loss of moisture.

3 Units

Code 123-93